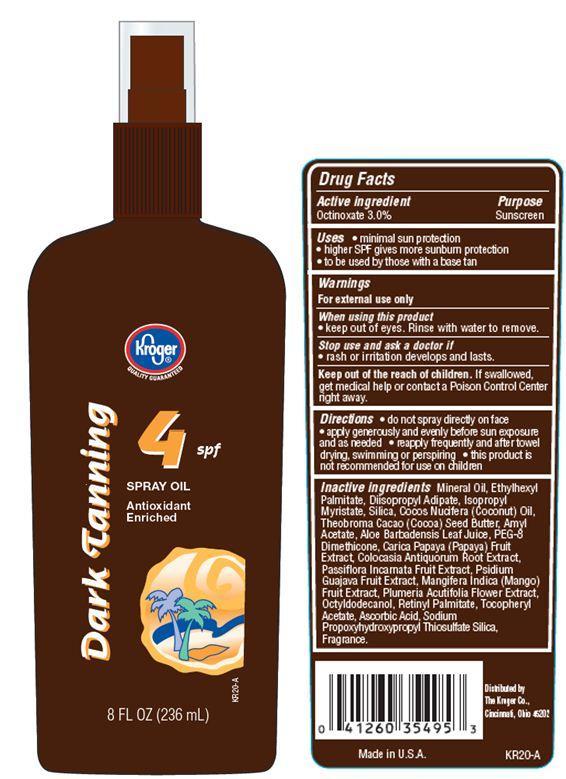 DRUG LABEL: Kroger Dark Tanning Oil
NDC: 30142-904 | Form: SPRAY
Manufacturer: THE KROGER CO
Category: otc | Type: HUMAN OTC DRUG LABEL
Date: 20121119

ACTIVE INGREDIENTS: OCTINOXATE 3 g/100 g
INACTIVE INGREDIENTS: MINERAL OIL; ETHYLHEXYL PALMITATE; DIISOPROPYL ADIPATE; ISOPROPYL MYRISTATE; SILICON DIOXIDE; COCONUT OIL; AMYL ACETATE; PAPAYA; COLOCASIA ESCULENTA ROOT; .ALPHA.-TOCOPHEROL ACETATE; PASSIFLORA INCARNATA FRUIT; GUAVA; COCOA BUTTER; MANGO; PEG-8 DIMETHICONE; ALOE VERA LEAF; OCTYLDODECANOL; VITAMIN A PALMITATE; ASCORBIC ACID; PLUMERIA RUBRA FLOWER

Drug Facts

Active ingredient

Octinoxate 3.0%

Purpose

Sunscreen

Uses

- minimal sun protection
- higher SPF gives more sunburn protection
- to be used by those with a base tan

Warnings

For external use only

When using this product

- keep out of eyes. Rinse with water to remove

Stop use and ask a doctor if

- rash or irritation develops and lasts.

Keep Out of the reach of children.

If swallowed get medical help or contact a Poison Control Center right away.

Directions

- do not spray directly on face
- apply generously and evenly before sun exposure and as needed
- reapply frequently and after towel drying, swimming or perspiring.
- this product is not recommended for use on children

Inactive ingredients

Mineral Oil, Isopropyl Myristate, Sesamum Indicum (Sesame) Seed Oil, Persea Gratissima (Avocado) Oil, Amyl Acetate, Cocos Nucifera (Coconut) Oil, Squalane, Tocopheryl Acetate, Aloe Barbadensis Leaf Extract, Aleurites Moluccana Seed Extract, Carica Papaya (Papaya) Fruit Extract, Colocasia Antiquorum Root Extract, Mangifera Indica (Mango) Fruit Extract, Passiflora Incarnata Fruit Extract, Plumeria Acutifolia Flower Extract, Psidium Guajava Fruit Extract, Eucalyptus Globulus Leaf Oil, Fragrance.

Principal Display Panel

kroger
QUALITY GUARANTEED
Dark Tanning
4 spf
SPRAY OIL
Antioxidant
Enriched
8 FL OZ(236 mL)